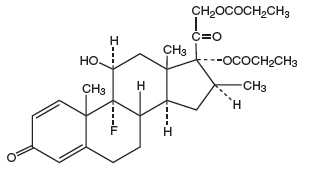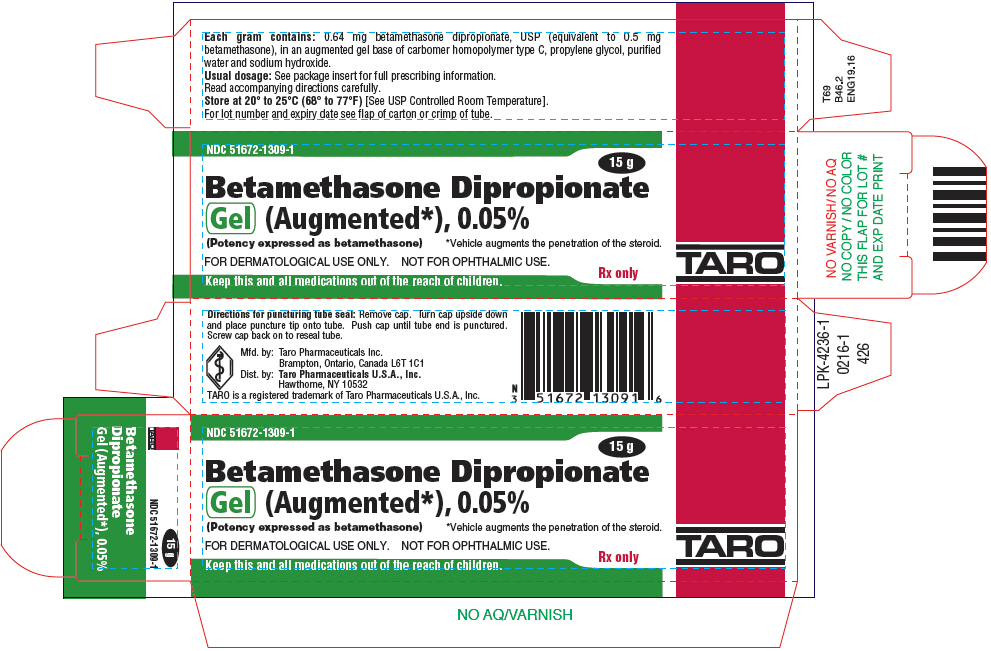 DRUG LABEL: Betamethasone Dipropionate
NDC: 51672-1309 | Form: GEL
Manufacturer: Sun Pharmaceutical Industries, Inc.
Category: prescription | Type: HUMAN PRESCRIPTION DRUG LABEL
Date: 20250702

ACTIVE INGREDIENTS: BETAMETHASONE DIPROPIONATE 0.5 mg/1 g
INACTIVE INGREDIENTS: CARBOMER HOMOPOLYMER TYPE C (ALLYL PENTAERYTHRITOL CROSSLINKED); PROPYLENE GLYCOL; WATER; SODIUM HYDROXIDE

Betamethasone Dipropionate
Gel (Augmented*), 0.05%

(Potency expressed as betamethasone)
*Vehicle augments the penetration of the steroid.

FOR DERMATOLOGICAL USE ONLY
NOT FOR OPHTHALMIC USE

Rx only

DESCRIPTION

Betamethasone dipropionate gel (augmented), 0.05%, contains betamethasone dipropionate, USP, a synthetic fluorinated corticosteroid for topical dermatologic use. Betamethasone dipropionate is included in a class of compounds consisting primarily of synthetic corticosteroids for use topically as anti-inflammatory and anti-pruritic agents.

Chemically, betamethasone dipropionate is 9-fluoro-11β,17,21-trihydroxy-16β-methylpregna-1,4-diene-3,20-dione 17,21-dipropionate, with the molecular formula C28H37FO7, a molecular weight of 504.6, and the following structural formula:

Betamethasone dipropionate is a white to creamy white, odorless crystalline powder, insoluble in water.

Each gram of betamethasone dipropionate gel (augmented) contains: 0.64 mg betamethasone dipropionate, USP (equivalent to 0.5 mg betamethasone), in an augmented gel base of carbomer homopolymer type C, propylene glycol, purified water and sodium hydroxide.

CLINICAL PHARMACOLOGY

Like other topical corticosteroids, betamethasone dipropionate has anti-inflammatory, anti-pruritic, and vasoconstrictive properties. The mechanism of the anti-inflammatory activity of the topical steroids, in general, is unclear. However, corticosteroids are thought to act by the induction of phospholipase A2inhibitory proteins, collectively called lipocortins. It is postulated that these proteins control the biosynthesis of potent mediators of inflammation, such as prostaglandins and leukotrienes, by inhibiting the release of their common pre-cursor, arachidonic acid. Arachidonic acid is released from membrane phospholipids by phospholipase A2.

Pharmacokinetics

The extent of percutaneous absorption of topical corticosteroids is determined by many factors including the vehicle and the integrity of the epidermal barrier. Occlusive dressings with hydrocortisone for up to 24 hours have not been demonstrated to increase penetration; however, occlusion of hydrocortisone for 96 hours markedly enhances penetration. Topical corticosteroids can be absorbed from normal intact skin. In addition, inflammation and/or other disease processes in the skin may increase percutaneous absorption. Studies performed with betamethasone dipropionate gel (augmented) indicate that it is in the super-high range of potency as compared with other topical corticosteroids.

INDICATIONS AND USAGE

Betamethasone dipropionate gel (augmented) is a super-high potency corticosteroid indicated for the relief of the inflammatory and pruritic manifestations of corticosteroid-responsive dermatoses. Treatment beyond two consecutive weeks is not recommended, and the total dose should not exceed 50 g per week because of potential for the drug to suppress the hypothalamic-pituitary-adrenal (HPA) axis.

This product is not recommended for use in pediatric patients under 12 years of age.

CONTRAINDICATIONS

Betamethasone dipropionate gel (augmented) is contraindicated in those patients with a history of hypersensitivity to any of the components of the preparation.

PRECAUTIONS

General

Betamethasone dipropionate gel (augmented) should not be used in the treatment of rosacea or perioral dermatitis, and it should not be used on the face, groin, or in the axillae.

Systemic absorption of topical corticosteroids can produce reversible hypothalamic-pituitary-adrenal (HPA) axis suppression with the potential for glucocorticosteroid insufficiency after withdrawal of treatment. Manifestations of Cushing's syndrome, hyperglycemia, and glucosuria can also be produced in some patients by systemic absorption of topical corticosteroids while on treatment.

At 7 g per day (applied once daily or as 3.5 g twice daily), betamethasone dipropionate gel (augmented) was shown to cause inhibition of the HPA axis following application for one, two or three weeks to diseased skin in some patients with psoriasis or atopic dermatitis. These effects were reversible upon discontinuation of treatment.

Patients receiving betamethasone dipropionate gel (augmented) applied to large areas should be evaluated periodically for evidence of HPA axis suppression. This may be done by using the ACTH-stimulation, morning plasma cortisol and urinary free-cortisol tests. Patients should not be treated with betamethasone dipropionate gel (augmented) for more than 2 weeks at a time, and amounts greater than 50 g per week should not be used because of the potential for the drug to suppress the HPA axis.

If HPA axis suppression is noted, an attempt should be made to withdraw the drug, to reduce the frequency of application, or to substitute a less potent corticosteroid. Recovery of HPA axis function is generally prompt and complete upon discontinuation of topical corticosteroids. Infrequently, signs and symptoms of glucocorticosteroid insufficiency may occur, requiring supplemental systemic corticosteroids. For information on systemic supplementation, see prescribing information for systemic corticosteroids.

Pediatric patients may be more susceptible to systemic toxicity from equivalent doses due to their larger skin surface to body mass ratios (see PRECAUTIONS - Pediatric Use).

If irritation develops, betamethasone dipropionate gel (augmented) should be discontinued and appropriate therapy instituted. Allergic contact dermatitis with corticosteroids is usually diagnosed by observing failure to heal rather than noting clinical exacerbation as with most topical products not containing corticosteroids. Such an observation should be corroborated with appropriate diagnostic patch testing.

If concomitant fungal and/or bacterial skin infections are present or develop, an appropriate antifungal or antibacterial agent should be used. If a favorable response does not occur promptly, use of betamethasone dipropionate gel (augmented) should be discontinued until the infection has been adequately controlled.

Information for Patients

Patients using topical corticosteroids should receive the following information and instructions:

1. The medication is to be used as directed by the physician. It is for external use only. Avoid contact with the eyes.
2. The medication should not be used for any disorder other than that for which it was prescribed.
3. The treated skin area should not be bandaged or otherwise covered or wrapped so as to be occlusive.
4. Patients should report to their physician any signs of local adverse reactions.

Laboratory Tests

The following tests may be helpful in evaluating patients for HPA axis suppression:

ACTH stimulation test, Morning plasma-cortisol test, Urinary free-cortisol test

Carcinogenesis, Mutagenesis, Impairment of Fertility

Long-term animal studies have not been performed to evaluate the carcinogenic potential of betamethasone dipropionate.

Studies in rabbits, mice and rats using intramuscular doses up to 1, 33 and 2 mg/kg, respectively, resulted in dose related increases in fetal resorptions in the rabbits and mice.

Pregnancy

Teratogenic Effects

Pregnancy Category C

Corticosteroids have been shown to be teratogenic in laboratory animals when administered systemically at relatively low dosage levels. Some corticosteroids have been shown to be teratogenic after dermal application to laboratory animals.

Betamethasone dipropionate has been shown to be teratogenic in rabbits when given by the intramuscular route at doses of 0.05 mg/kg. This dose is approximately 26 times the human topical dose of betamethasone dipropionate gel (augmented) assuming human percutaneous absorption of approximately 3% and the use in a 70 kg person of 7 g per day. The abnormalities observed included umbilical hernias, cephalocele, and cleft palate.

There are no adequate and well-controlled studies of the teratogenic potential of betamethasone dipropionate in pregnant women. Therefore, betamethasone dipropionate gel (augmented) should be used during pregnancy only if the potential benefit justifies the potential risk to the fetus.

Nursing Mothers

Systemically administered corticosteroids appear in human milk and could suppress growth, interfere with endogenous corticosteroid production, or cause other untoward effects. It is not known whether topical administration of corticosteroids could result in sufficient systemic absorption to produce detectable quantities in human milk. Because many drugs are excreted in human milk, caution should be exercised when betamethasone dipropionate gel (augmented) is administered to a nursing woman.

Pediatric Use

Data regarding use of betamethasone dipropionate gel (augmented) in pediatric patients are not available, so use of this product in patients under the age of 12 is not recommended. Because of a higher ratio of skin surface area to body mass, pediatric patients are at a greater risk than adults of HPA axis suppression when they are treated with topical corticosteroids. They are, therefore, also at greater risk of glucocorticosteroid insufficiency after withdrawal of treatment and of Cushing's syndrome while on treatment.Adverse effects, including striae, have been reported with inappropriate use of topical corticosteroids in infants and pediatric patients.

HPA axis suppression, Cushing's syndrome, and intracranial hypertension have been reported in pediatric patients receiving topical corticosteroids. Manifestations of adrenal suppression in pediatric patients include linear growth retardation, delayed weight gain, low plasma cortisol levels, and absence of response to ACTH stimulation. Manifestations of intracranial hypertension include bulging fontanelles, headaches, and bilateral papilledema.

Geriatric Use

Clinical studies of betamethasone dipropionate gel (augmented) included 65 subjects who were 65 years of age and over and 15 subjects who were 75 years of age and over. No overall differences in safety or effectiveness were observed between these subjects and younger subjects, and other reported clinical experience has not identified differences in responses between the elderly and younger patients. However, greater sensitivity of some older individuals cannot be ruled out.

ADVERSE REACTIONS

In controlled clinical trials, the total incidence of adverse events associated with the use of betamethasone dipropionate gel (augmented) was 10%. These included stinging or burning in 6% of patients, dry skin in 4% of patients, and pruritus in 2% of patients. Less frequently reported adverse reactions were irritation, skin atrophy, telangiectasia, erythema, cracking/tightening of the skin, follicular rash, and allergic contact dermatitis.

The following additional local adverse reactions are reported infrequently with topical corticosteroids, but may occur more frequently with super-high potency corticosteroids, such as betamethasone dipropionate gel (augmented).

These reactions are listed in approximate decreasing order of occurrence: acneiform eruptions, hypopigmentation, perioral dermatitis, secondary infection, striae, and miliaria.

OVERDOSAGE

Topically applied betamethasone dipropionate gel (augmented) can be absorbed in sufficient amounts to produce systemic effects (see PRECAUTIONS).

DOSAGE AND ADMINISTRATION

Apply a thin layer of betamethasone dipropionate gel (augmented) to the affected skin once or twice daily and rub it in gently and completely.

Betamethasone dipropionate gel (augmented) is a super-high potency topical corticosteroid; therefore, treatment should be limited to two weeks, and amounts greater than 50 g per week should not be used.

Betamethasone dipropionate gel (augmented) should not be used with occlusive dressings.

HOW SUPPLIED

Betamethasone Dipropionate Gel (Augmented), 0.05% is supplied as follows:

 | 15 g | NDC 51672-1309-1
 | 50 g | NDC 51672-1309-3

STORAGE AND HANDLING

Store at 20° to 25°C (68° to 77°F)[See USP Controlled Room Temperature].

Mfd. by: Taro Pharmaceuticals Inc., Brampton, Ontario, Canada L6T 1C1
Dist. by: Taro Pharmaceuticals U.S.A., Inc.,Hawthorne, NY 10532
PK-4240-1
0116-1 28

PRINCIPAL DISPLAY PANEL - 15 g Tube Carton

NDC 51672-1309-1

15 g

Betamethasone Dipropionate
Gel (Augmented*), 0.05%
(Potency expressed as betamethasone)
*Vehicle augments the penetration of the steroid.

FOR DERMATOLOGICAL USE ONLY. NOT FOR OPHTHALMIC USE.

Rx only

Keep this and all medications out of the reach of children.

TARO